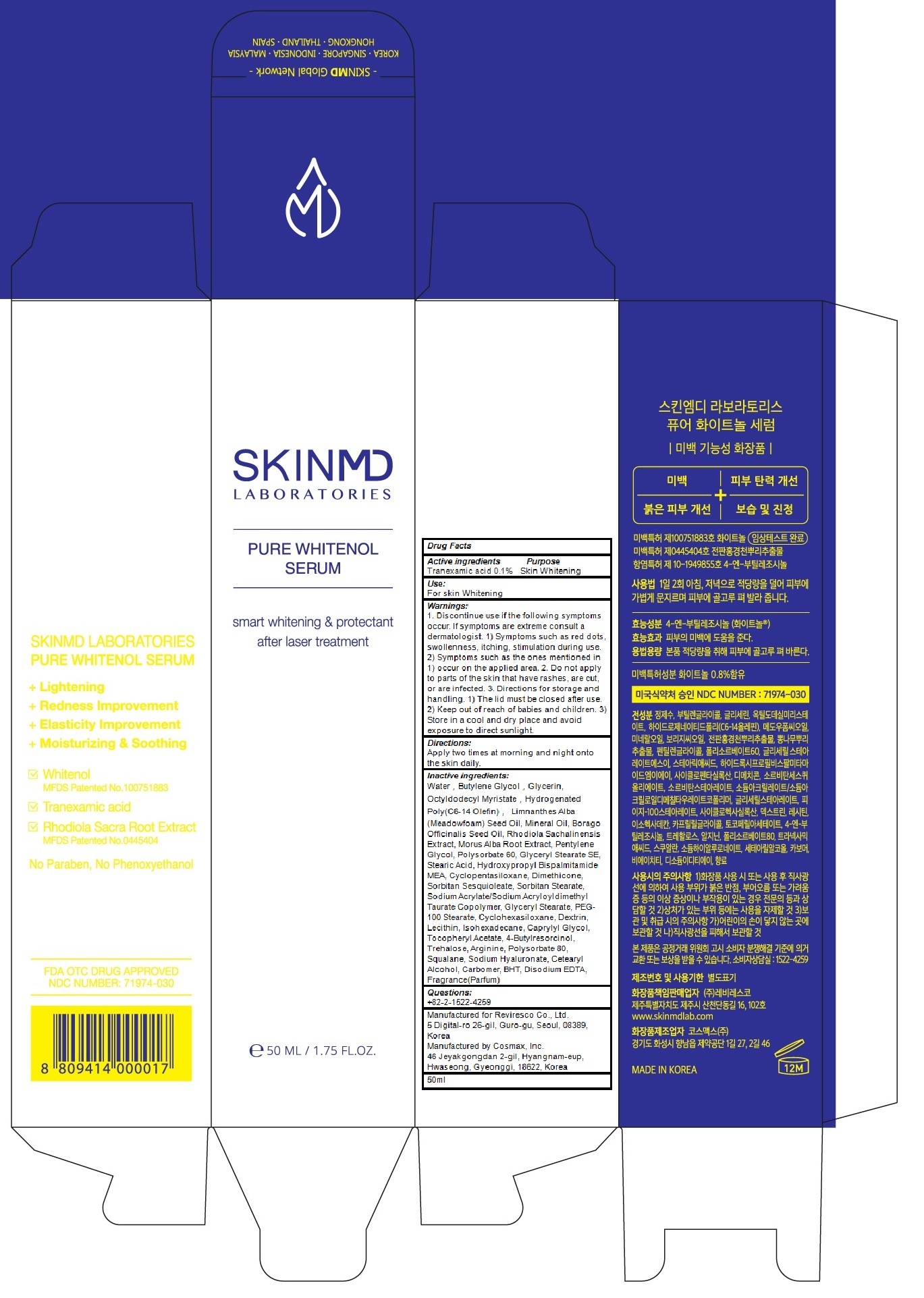 DRUG LABEL: SKINMD LABORATORIES PURE WHITENOL SERUM
NDC: 71974-030 | Form: CREAM
Manufacturer: Reviresco Co., Ltd.
Category: otc | Type: HUMAN OTC DRUG LABEL
Date: 20191224

ACTIVE INGREDIENTS: Tranexamic acid 0.05 g/50 mL
INACTIVE INGREDIENTS: Water; Butylene Glycol

ACTIVE INGREDIENT

Active ingredients: Tranexamic acid 0.1%

INACTIVE INGREDIENT

Inactive ingredients:

Water，Butylene Glycol，Glycerin, Octyldodecyl Myristate，Hydrogenated Poly(C6-14 Olefin)， Limnanthes Alba (Meadowfoam) Seed Oil, Mineral Oil, Borago Officinalis Seed Oil, Rhodiola Sachalinensis Extract, Morus Alba Root Extract, Pentylene Glycol, Polysorbate 60, Glyceryl Stearate SE, Stearic Acid, Hydroxypropyl Bispalmitamide MEA, Cyclopentasiloxane, Dimethicone, Sorbitan Sesquioleate, Sorbitan Stearate, Sodium Acrylate/Sodium Acryloyldimethyl Taurate Copolymer, Glyceryl Stearate, PEG-100 Stearate, Cyclohexasiloxane, Dextrin, Lecithin, Isohexadecane, Caprylyl Glycol, Tocopheryl Acetate, 4-Butylresorcinol, Trehalose, Arginine, Polysorbate 80, Squalane, Sodium Hyaluronate, Cetearyl Alcohol, Carbomer, BHT, Disodium EDTA, Fragrance(Parfum)

PURPOSE

Purpose: Skin Whitening

WARNINGS

1. Discontinue use if the following symptoms occur. If symptoms are extreme consult a dermatologist. 1) Symptoms such as red dots, swollenness, itching, stimulation during use. 2) Symptoms such as the ones mentioned in 1) occur on the applied area. 2. Do not apply to parts of the skin that have rashes, are cut, or are infected. 3. Directions for storage and handling. 1) The lid must be closed after use. 2) Keep out of reach of babies and children. 3) Store in a cool and dry place and avoid exposure to direct sunlight.

KEEP OUT OF REACH OF CHILDREN

Keep out of reach of babies and children.

Uses

Uses: For skin Whitening

Directions

Directions: Apply two times at morning and night onto the skin daily.